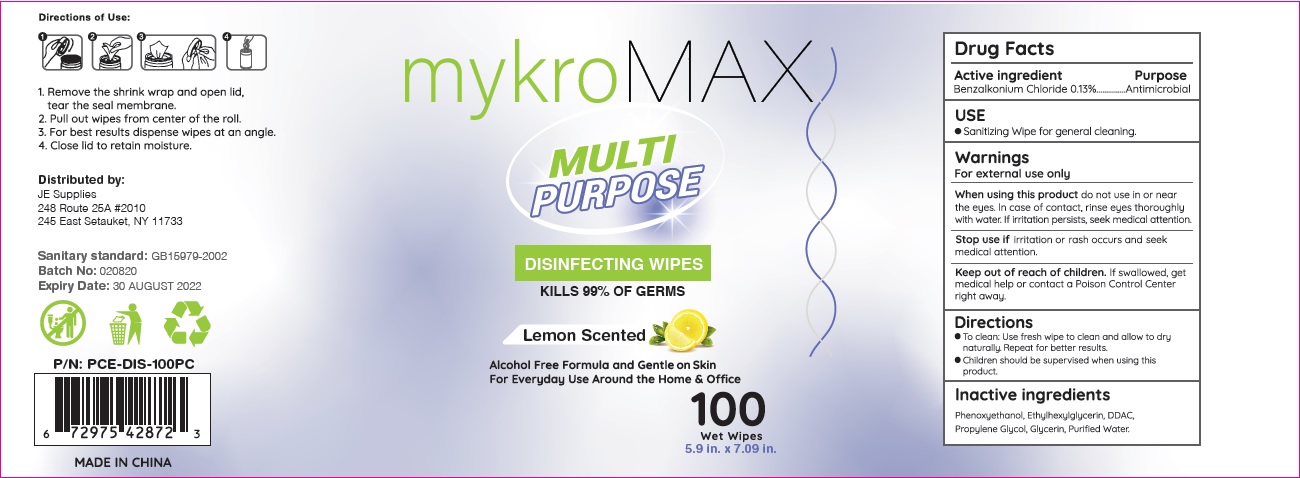 DRUG LABEL: Mykro Max Multi Purpose  Disinfecting  wipe
NDC: 71734-322 | Form: SWAB
Manufacturer: JIANGMEN SHUIZIRUN SANITARY ARTICLES CO., LTD.
Category: otc | Type: HUMAN OTC DRUG LABEL
Date: 20200731

ACTIVE INGREDIENTS: benzalkonium chloride 0.13 g/100 g
INACTIVE INGREDIENTS: water; PHENOXYETHANOL; ETHYLHEXYLGLYCERIN; PROPYLENE GLYCOL; GLYCERIN

DRUG FACTS

Active Ingredient

Benzalkonium Chloride .......... 0.13 %

Purpose

Antiseptic

Uses:

sanitizing wipe for general cleaning.

Warnings

For external use only.

When using this product do not use in or near the eyes. In case of contact, rinse eyes thoroughly with water.

Stop use and ask a doctor if irritation persists, seek edical attention.

Keep out of reach of children.

if swallowed get medical help or contact a Poison Control Center right away.

Directions

- To clean: use fresh wipe to clan and allow to dry naturally. Repeat for better results.
- Children should be supervised when using this product.

Inactive Ingredients:

Phenoxyethanol, Ethylhexylglycerin, DDAC, Propylene Glycol, Glycerin, Purified Water.